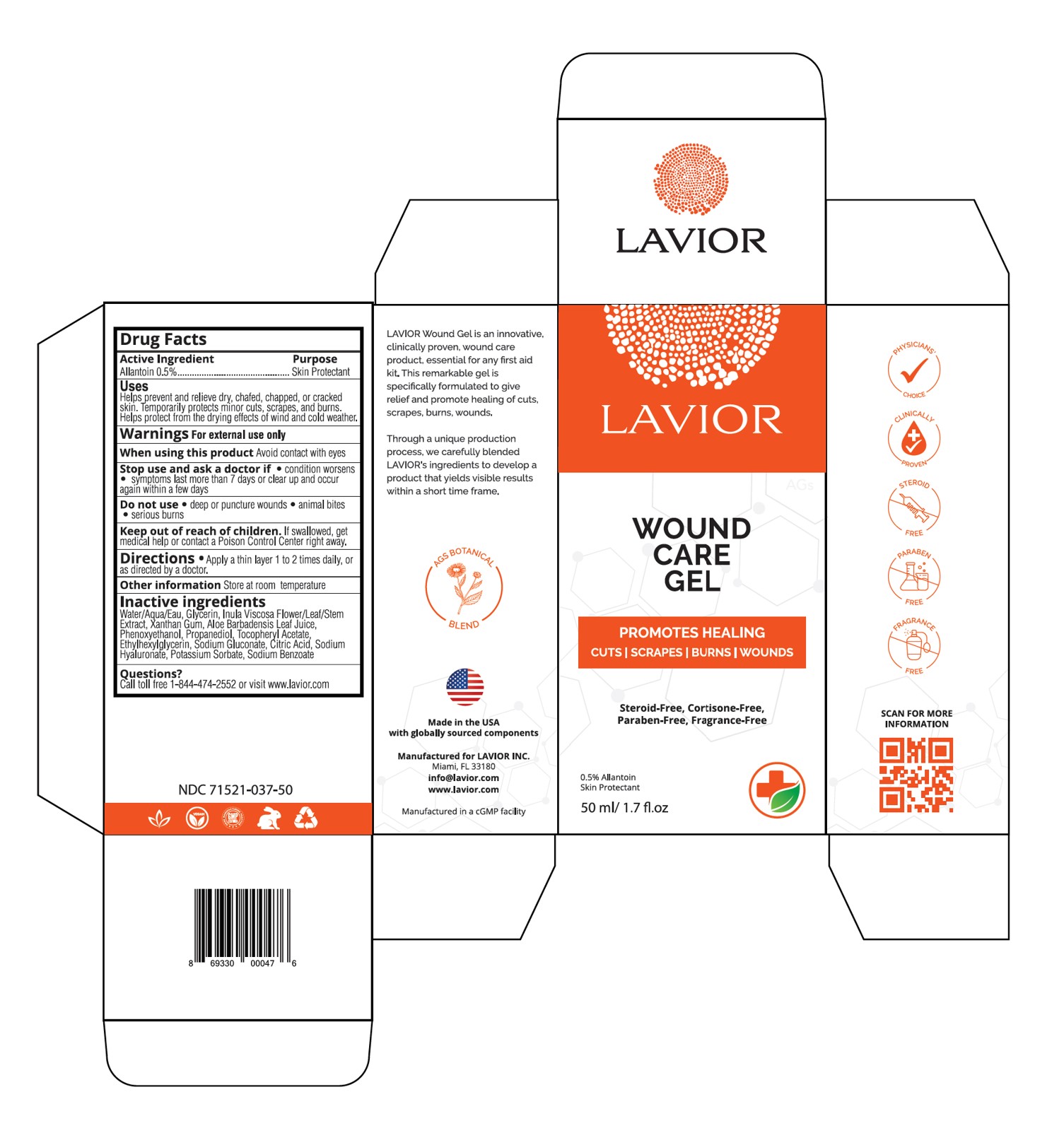 DRUG LABEL: Wound Gel
NDC: 71521-037 | Form: GEL
Manufacturer: Lavior Pharma Inc
Category: otc | Type: HUMAN OTC DRUG LABEL
Date: 20241022

ACTIVE INGREDIENTS: ALLANTOIN 0.5 g/100 g
INACTIVE INGREDIENTS: ETHYLHEXYLGLYCERIN; SODIUM GLUCONATE; CITRIC ACID MONOHYDRATE; SODIUM BENZOATE; HYALURONATE SODIUM; POTASSIUM SORBATE; XANTHAN GUM; ALOE VERA LEAF; PHENOXYETHANOL; PROPANEDIOL; .ALPHA.-TOCOPHEROL ACETATE, DL-; DITTRICHIA VISCOSA WHOLE; GLYCERIN

Active Ingredient

Allantoin 0.5%................................Skin Protectant

Purpose

Skiin Protectant

Uses

- helps prevent and relieve dry, chafed, chapped, or cracked skin
- temporarily protects minor cuts, scrapes, and burns
- helps protect from the drying effects of wind and cold weather

Warnings

For external use only

When using this product

- avoid contact with eyes

Stop use and ask a doctor if

- condition worsens
- symptoms last more than 7 days clear up and occur again within a few days

Do not use

- deep or puncture wounds
- animal bites
- serious burns

Keep out of reach of children

If swallowed, get medical help or contact a Poison Control Center right away.

Directions

- apply a thin layer 1 to 2 times daily, or as directed by a doctor

Other information

Store at room temperature

Inactive Ingredients

Water/Aqua/Eau, Glycerin, Inula Viscosa Flower/Leaf/Stem Extract, Xanthan Gum, Aloe Barbadensis Leaf Juice, Phenoxyethanol, Propanediol, Tocopheryl Acetate, Ethylhexylglycerin, Sodium Gluconate, Citric Acid, Sodium Hyaluronate, Potassium Sorbate, Sodium Benzoate

Questions?

Call (305) 627-3680 or visit www.lavior.com